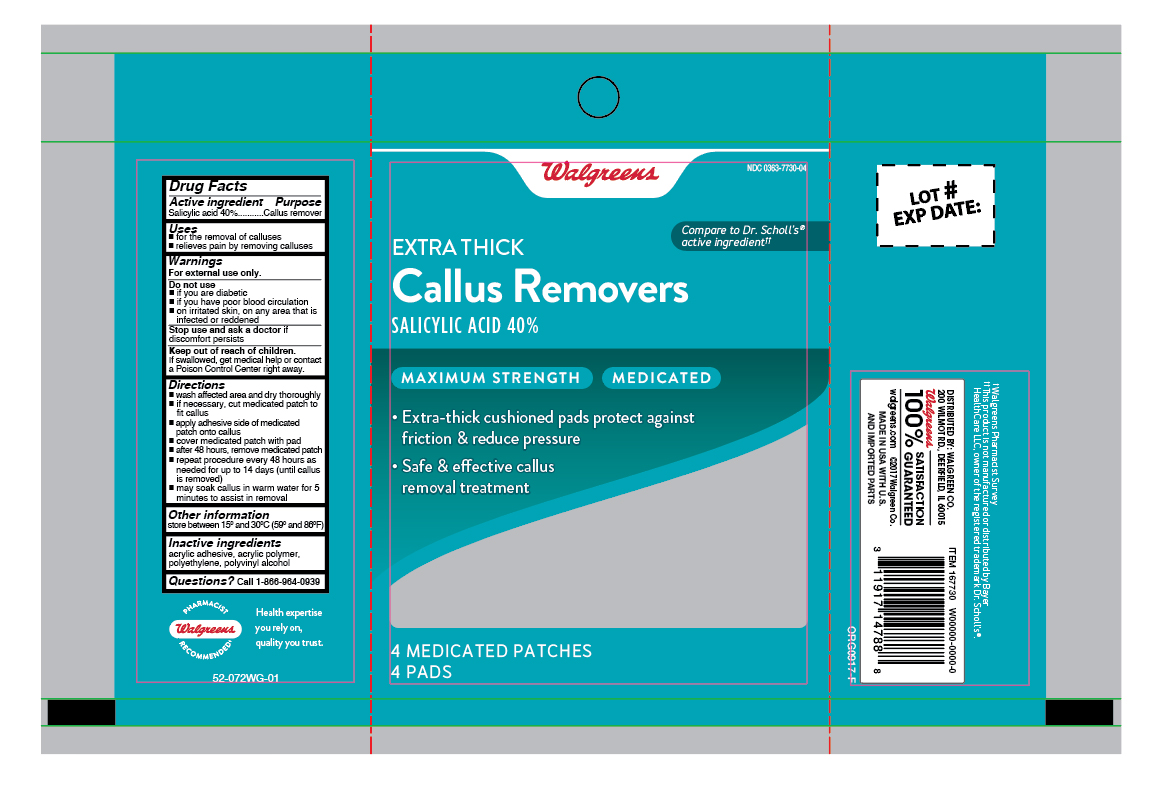 DRUG LABEL: Salicylic Acid
NDC: 0363-7730 | Form: PATCH
Manufacturer: Walgreen Company
Category: otc | Type: HUMAN OTC DRUG LABEL
Date: 20260120

ACTIVE INGREDIENTS: SALICYLIC ACID 40 mg/4 1
INACTIVE INGREDIENTS: POLYVINYL ALCOHOL; HIGH DENSITY POLYETHYLENE

Walgreens Extra Thick Callus Removers

Active ingredient

Salicylic acid 40%

Purpose

Callus remover

Uses

- for the removal of calluses
- relieves pain by removing calluses

Warnings

For external use only.

Do not use

- if you are a diabetic
- if you have poor blood circulation
- on irritated skin, or any area that is infected or reddened

Stop use and ask a doctor

if discomforts persists

Keep out of reach of children.

If swallowed, get medical help or contact a Poison Control Center right away.

Directions

- wash affected area and dry thoroughly
- if necessary, cut medicated patch to fit callus
- apply adhesive side of medicated patch onto callus
- cover medicated patch with pad
- after 48 hours, remove medicated patch
- repeat procedure every 48 hours as needed for up to 14 days (until callus is removed)
- may soak callus in warm water for 5 minutes to assist in removal

Other information

store between 15°C to 30°C (59°F to 86°F)

Inactive ingredients

acrylic adhesive, acrylic polymer, polyethylene, polyvinyl alcohol

Questions?

call 1-866-964-0939

RECENT MAJOR CHANGES

.

Principal Display Panel

Well at Walgreens

NEW!

Extra Thick
Callus Removers
Salicylic acid

- Safe & effective Callus removal treatment
- Provides cushion & comfort

4 Pads

4 Medicated Patches